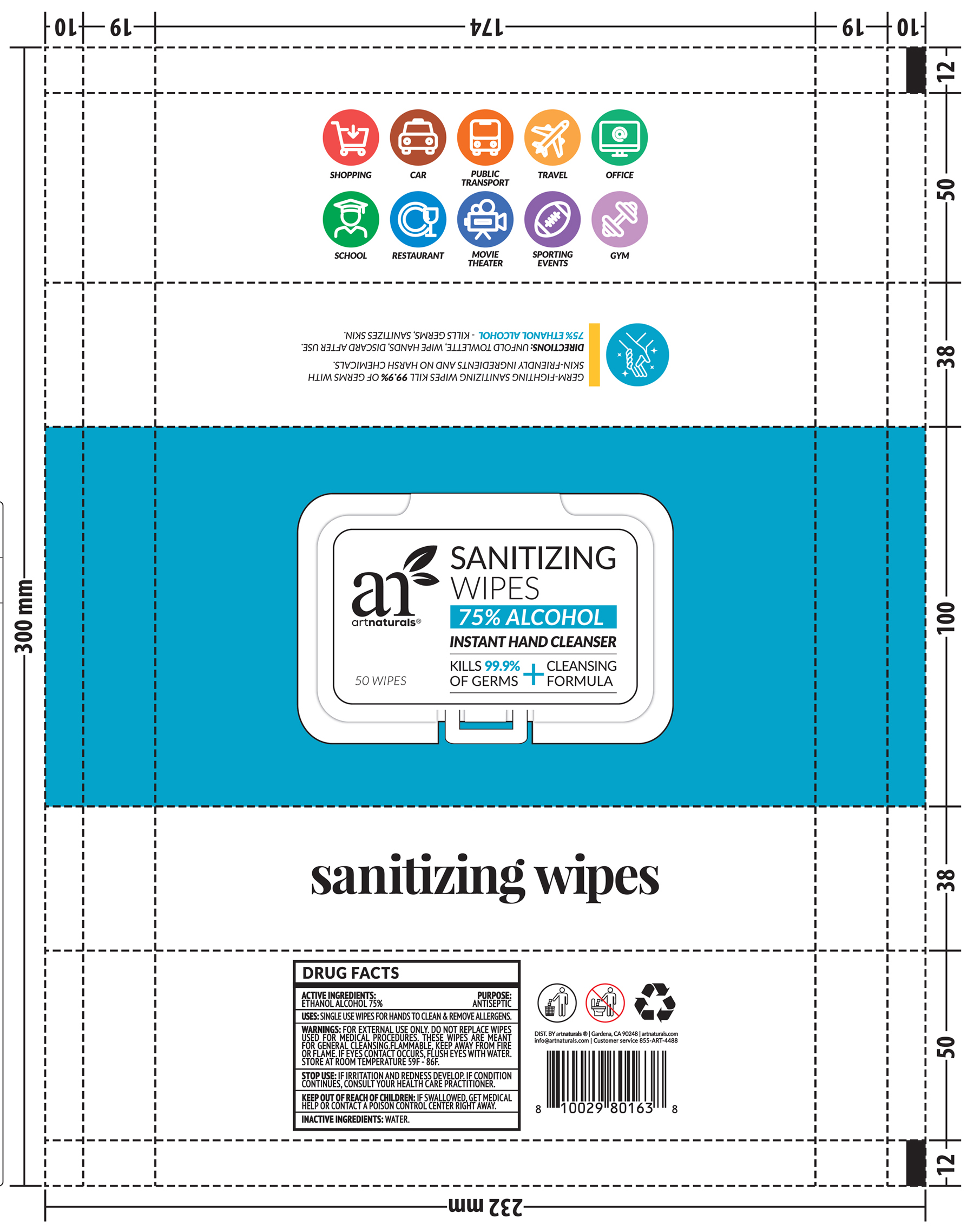 DRUG LABEL: sanitizing wipes
NDC: 74642-003 | Form: CLOTH
Manufacturer: Virgin Scent Inc.
Category: otc | Type: HUMAN OTC DRUG LABEL
Date: 20200625

ACTIVE INGREDIENTS: ALCOHOL 0.75 mL/1 1
INACTIVE INGREDIENTS: WATER

sanitizing wipes

Active Ingredient(s)

Alcohol 75%. Purpose: Antiseptic

Purpose

Antiseptic

Use

Single use wipes for hands to clean & remove allergen.

Warnings

For external use only. Do not replace wipes used for medical procedures. These wipes are meant for general cleansing.Flammable. Keep away from heat or flame.

Do not use

if eye contact occurs, flush eyes with water.

Stop use

if irritation and redness develop. If condition continues, consult your health care practitioner

Keep out of reach of children. If swallowed, get medical help or contact a Poison Control Center right away.

Directions

Unfold towlette, wipe hands, discard after use.

75% ETHANOL ALCOHOL- kills germs, sanitizes skin.

Other information

Store at room temperature 59F-86F

Inactive ingredients

water

RECENT MAJOR CHANGES

- Indications and Usage
- Dosage and Administration

Package Label - Principal Display Panel

50 PCS NDC: 74642-003-01